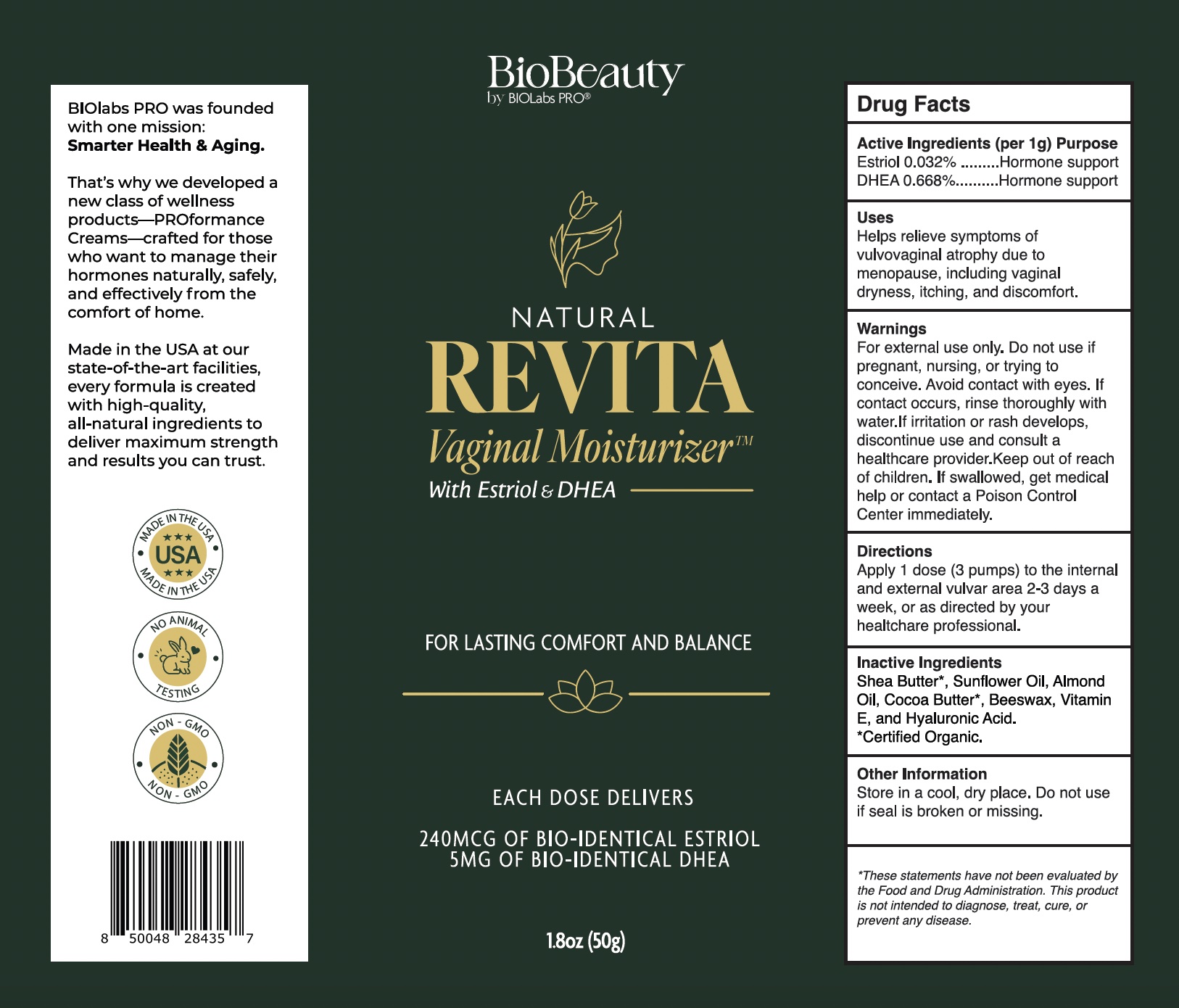 DRUG LABEL: Natural Revita Vaginal Moisturizer
NDC: 82018-0025 | Form: CREAM
Manufacturer: Shyne Brands/BIOLabs PRO
Category: otc | Type: HUMAN OTC DRUG LABEL
Date: 20250601

ACTIVE INGREDIENTS: ESTRIOL 0.08 mg/51000 mg
INACTIVE INGREDIENTS: ALMOND OIL 1 mg/51000 mg; SHEA BUTTER 1 mg/51000 mg; BEESWAX 1 mg/51000 mg; SUNFLOWER OIL 1 mg/51000 mg; VITAMIN E POLYETHYLENE GLYCOL SUCCINATE 1 mg/51000 mg; HYALURONIC ACID 1 mg/51000 mg; COCOA BUTTER 1 mg/51000 mg

Natural Revita Vaginal Moisturizer

DRUG FACTS
Active Ingredients (per 1g):
Estriol .032%

Dhea .668%

PURPOSE

Natural Vaginal Moisturizer for women with bioidentical Estriol and Dhea.

Uses
Helps relieve symptoms of vulvovaginal atrophy due to menopause, including vaginal dryness, itching, and discomfort.

Warnings

For external use only. Do not use if pregnant, nursing, or trying to conceive. Avoid contact with eyes. If contact occurs, rinse thoroughly with water.If irritation or rash develops, discontinue use and consult a healthcare provider.Keep out of reach of children. If swallowed, get medical help or contact a Poison Control Center immediately.

PREGNANCY OR BREAST FEEDING

If pregnant or nursing or if you have a serious medical condition consult a healthcare professional before using this product.

Keep Out of Reach of Children.

Directions

Apply 1 dose (3 pumps) to the internal and external vulvar area 2-3 days a week, or as directed by your healtchare professional.

Inactive Ingredients

Shea Butter', Sunflower Oil, Almond Oil, Cocoa Butter·, Beeswax, Vitamin E, and Hyaluronic Acid.

·certified Organic.

Questions?
care@biolabspro.com
www.biolabspro.com